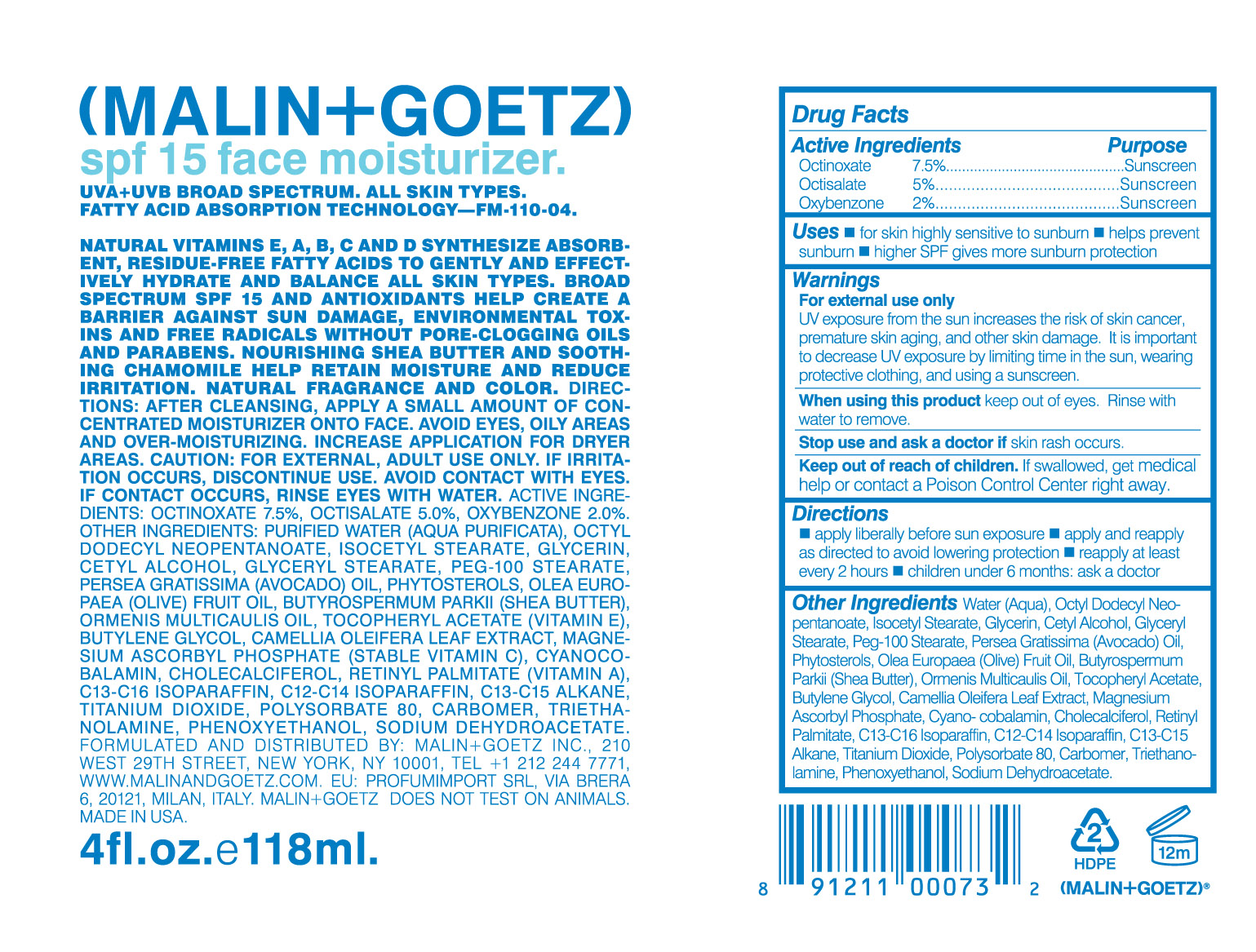 DRUG LABEL: 
                           
NDC: 53634-152 | Form: CREAM
Manufacturer: Malin & Goetz Inc
Category: otc | Type: HUMAN OTC DRUG LABEL
Date: 20121102

ACTIVE INGREDIENTS: OCTINOXATE 7.5 g/100 mL; OCTISALATE 5 g/100 mL; OXYBENZONE 2 g/100 mL
INACTIVE INGREDIENTS: WATER; ISOCETYL STEARATE; GLYCERIN; CETYL ALCOHOL; GLYCERYL MONOSTEARATE; PEG-100 STEARATE; AVOCADO OIL; OLIVE OIL; SHEA BUTTER; CLADANTHUS MIXTUS FLOWER VOLATILE OIL; .ALPHA.-TOCOPHEROL ACETATE; BUTYLENE GLYCOL; CAMELLIA OLEIFERA LEAF; MAGNESIUM ASCORBYL PHOSPHATE; CHOLECALCIFEROL; VITAMIN A PALMITATE; C13-16 ISOPARAFFIN; C13-15 ALKANE; TITANIUM DIOXIDE; POLYSORBATE 80; CARBOMER 934; trolamine; PHENOXYETHANOL; SODIUM DEHYDROACETATE

SPF 15 face moisturizer

Active ingredients purpose

Octinoxate 7.5% Sunscreen

Octisalate 5% Sunscreen

Oxybenzone 2% Sunscreen

Uses

For skin highly sensitive for sunburn

helps prevent sunburn

higher SPF gives more sunburn protection

Keep out of reach of children. If product is swallowed, get medical help or
contact a Poison Control Center right away.

Stop use and ask a doctor if skin rash occurs

Warnings

For external use only

UV exposure from the sun increases the risk of skin cancer, premature skin aging, and other skin damage. It is important to decrease UV exposure by limiting time in the sun, wearing protective clothin and using a sunscreen

Directions
Apply liberally before sun exposure. Apply and reapply as directed to avoid lowering protection.
Reapply at least every 2 hours. Children under 6 months: Ask a doctor

INACTIVE INGREDIENT

Water (Aqua), Octyl Dodecyl Neopentanoate, Isocetyl stearate, glycerin, cetyl alcohol, glyceryl stearate, PEG-100 Stearate, Persea Gratissima (Avocado) Oil, Phytosterols, Olea Europaea (olive) Fruit oil, Butyrospermum Parkii (Shea butter), Ormenis Multicaulis, Tocopheryl Acetate, Butylene Glycol, Camellia Oleifera Leaf Extract, Magnesium Ascorbyl Phosphate, Cyano-cobalamin, Cholecalciferol, Retinyl Palmitate, C13-C16 Isoparaffin, C12-C14 Isoparaffin, C13-C15 Alkane, Titanium Dioxide, Polysorbate 80, Carbomer, Triethanolamine, phenoxyethanol, Sodium Dehydroacetate.

PACKAGE LABEL

(Malin + Goetz)

spf 15 face moisturizer.

UVA +UVB Broad Spectrum. All skin types. Fatty Acid Absorption technology-FM-110-04

4 fl. oz. e 118ml.